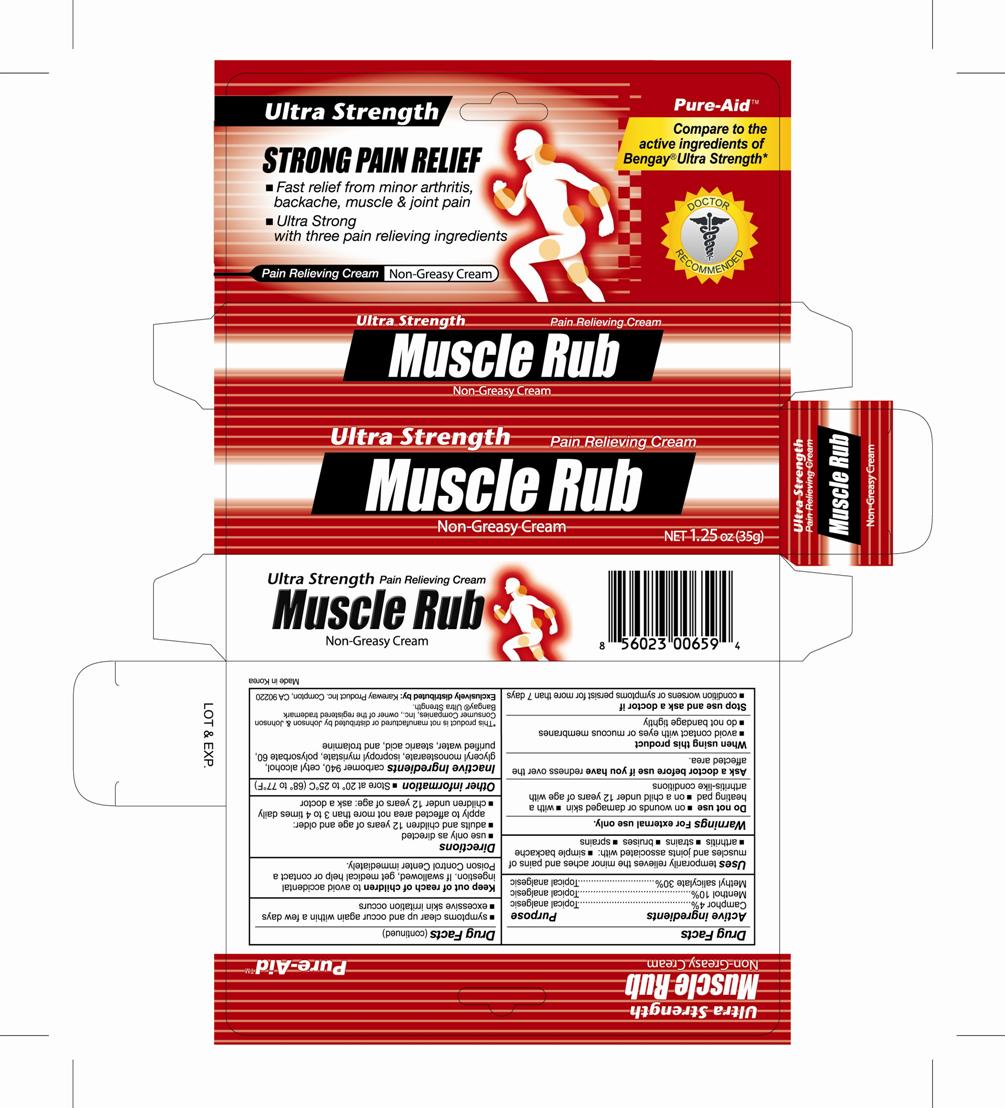 DRUG LABEL: Muscle Rub Ultra
NDC: 67510-0659 | Form: CREAM
Manufacturer: Kareway Product, Inc.
Category: otc | Type: HUMAN OTC DRUG LABEL
Date: 20230217

ACTIVE INGREDIENTS: MENTHOL 10 g/100 g; MENTHYL SALICYLATE, (+/-)- 30 g/100 g; CAMPHOR (NATURAL) 4 g/100 g
INACTIVE INGREDIENTS: EDETATE DISODIUM; GLYCERYL MONOSTEARATE; LANOLIN; POLYSORBATE 80; POTASSIUM HYDROXIDE; STEARIC ACID; TROLAMINE; WATER

Pure-Aid Muscle Rub Ultra

Active Ingredients

Camphor 4%

Menthol 10%

Methyl Salicylate 30%

Uses

temporarily relieves the minor aches and pains of muscle and joints associated with:

- simple bachache
- arthritis
- strains
- bruises
- sprains

WARNINGS

For external use only.

Do not use

- on wounds or damaged skin
- with a heating pad
- on a child under 12 years of age with arthritis-like conditions

Ask a doctor before use if you have

redness over the affected area

When using this product

- avoid contact with eyes or mucous membranes
- do not bandage tightly

Stop use and ask a doctor if

- condition worsens or symptoms persist for more than 7 days
- symptoms clear up and occur again within a few days
- excessive skin irritation occurs

Keep out of reach of children to avoid accidental ingestion.

If swallowed, get medical help or contact a Poison Control Center immediately

Directions

- Use only as directed

adults and children 12 years of age and older:

apply to affected area not more than 3 to 4 times daily

- children under 12 years of age: ask a doctor

Other information

- Store at 20° to 25°C (68°to 77° F)

Inactive Ingredients

carbomer, edetate disodium, glyceryl stearate se, lanolin, polysorbate 80, potassium hydroxide, purified water, stearic acid, trolamine

Questions?

call 1-800-883-0085, weekdays, 9AM -5PM PST

PURPOSE

Topical analgesic

Topical analgesic

Topical analgesic

PACKAGE LABEL

Muscle Rub Ultra